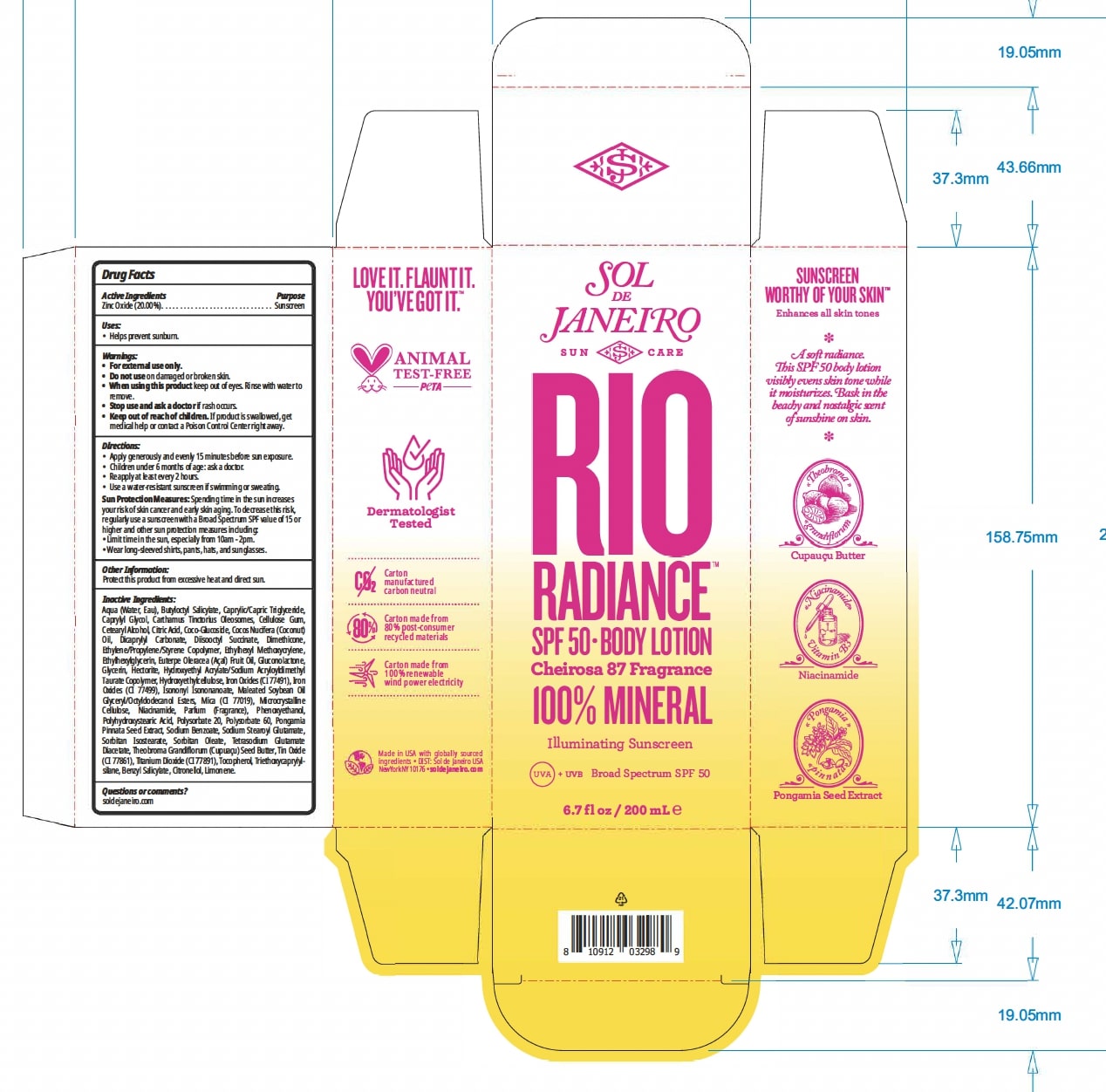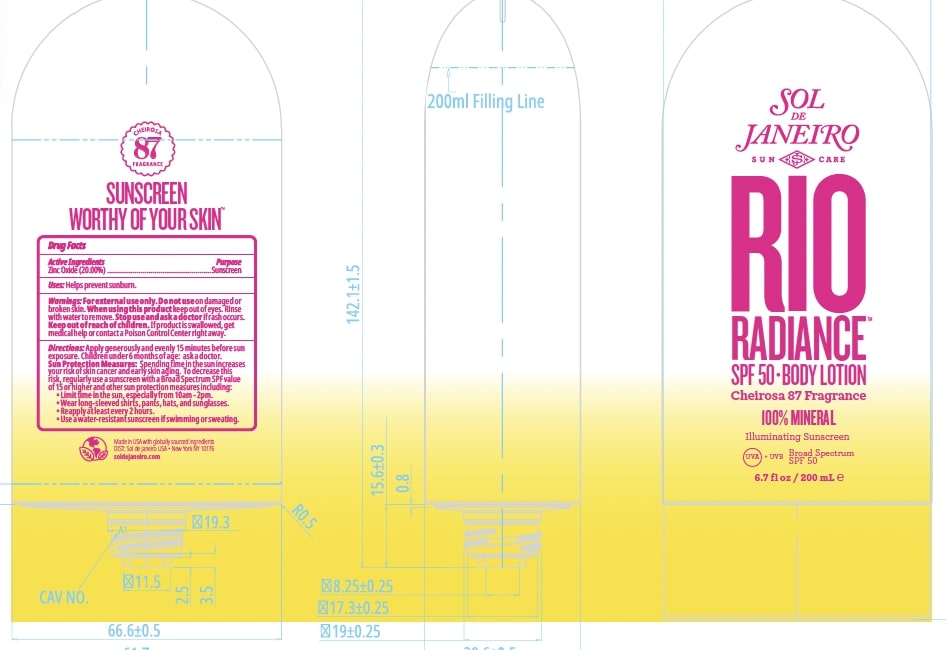 DRUG LABEL: Rio Radiance SPF 50 BodyLotion
NDC: 83982-4838 | Form: LOTION
Manufacturer: SOL DE JANEIRO USA, INC.
Category: otc | Type: HUMAN OTC DRUG LABEL
Date: 20240327

ACTIVE INGREDIENTS: ZINC OXIDE 20 g/100 mL
INACTIVE INGREDIENTS: TRIETHOXYCAPRYLYLSILANE; NIACINAMIDE; GLYCERIN; COCO GLUCOSIDE; PONGAMIA PINNATA SEED; HECTORITE; SAFFLOWER OIL; TETRASODIUM GLUTAMATE DIACETATE; ANHYDROUS CITRIC ACID; ETHYLHEXYLGLYCERIN; FERRIC OXIDE RED; DICAPRYLYL CARBONATE; HYDROXYETHYL ACRYLATE/SODIUM ACRYLOYLDIMETHYL TAURATE COPOLYMER (45000 MPA.S AT 1%); DIMETHICONE; ETHYLHEXYL METHOXYCRYLENE; SORBITAN MONOOLEATE; MEDIUM-CHAIN TRIGLYCERIDES; POLYSORBATE 60; STANNIC OXIDE; SODIUM STEAROYL GLUTAMATE; COCONUT OIL; CAPRYLYL GLYCOL; SORBITAN ISOSTEARATE; CETOSTEARYL ALCOHOL; TITANIUM DIOXIDE; MICA; TOCOPHEROL; THEOBROMA GRANDIFLORUM SEED BUTTER; ISONONYL ISONONANOATE; ACAI OIL; HYDROXYETHYL CELLULOSE, UNSPECIFIED; GLUCONOLACTONE; SODIUM BENZOATE; WATER; BUTYLOCTYL SALICYLATE; POLYSORBATE 20; PHENOXYETHANOL; CARBOXYMETHYLCELLULOSE SODIUM, UNSPECIFIED FORM; POLYHYDROXYSTEARIC ACID (2300 MW); MICROCRYSTALLINE CELLULOSE

Drug Facts

Active Ingredients Purpose

Zinc Oxide (20.00%)......Sunscreen

Dosage: Evenly and generously apply to skin.

Administration: Topical

Warnings:
• For external use only.
• Do not use on damaged or broken skin.
• When using this product keep out of eyes. Rinse with water to
remove.
• Stop use and ask a doctor if rash occurs.
• Keep out of reach of children. If product is swallowed, get
medical help or contact a Poison Control Center right away.

Sun Protection Measures: Spending time in the sun increases

your risk of skin cancer and early skin aging. To decrease this risk,

regularly use a sunscreen with a Broad Spectrum SPF value of 15 or

higher and other sun protection measures including:

• Limit time in the sun, especially from 10am - 2pm.

• Wear long-sleeved shirts, pants, hats, and sunglasses.

INACTIVE INGREDIENT

Aqua (Water, Eau), Butyloctyl Salicylate, Caprylic/Capric Triglyceride, Caprylyl Glycol, Carthamus Tinctorius Oleosomes, Cellulose Gum, Cetearyl Alcohol, Citric Acid, Coco-Glucoside, Cocos Nucifera (Coconut) Oil, Dicaprylyl Carbonate, Diisooctyl Succinate, Dimethicone, Ethylene/Propylene/Styrene Copolymer, Ethylhexyl Methoxycrylene, Ethylhexylglycerin, Euterpe Oleracea (Açaí) Fruit Oil, Gluconolactone, Glycerin, Hectorite, Hydroxyethyl Acrylate/Sodium Acryloyldimethyl Taurate Copolymer, Hydroxyethylcellulose, Iron Oxides (CI 77491), Iron Oxides (CI 77499), Isononyl Isononanoate, Maleated Soybean Oil Glyceryl/Octyldodecanol Esters, Mica (CI 77019), Microcrystalline Cellulose, Niacinamide, Parfum (Fragrance), Phenoxyethanol, Polyhydroxystearic Acid, Polysorbate 20, Polysorbate 60, Pongamia Pinnata Seed Extract, Sodium Benzoate, Sodium Stearoyl Glutamate, Sorbitan Isostearate, Sorbitan Oleate, Tetrasodium Glutamate Diacetate, Theobroma Grandiflorum (Cupuaçu) Seed Butter, Tin Oxide (CI 77861), Titanium Dioxide (CI 77891), Tocopherol, Triethoxycaprylylsilane, Benzyl Salicylate, Citronellol, Limonene.

Uses:

• Helps prevent sunburn.

Directions:

• Apply generously and evenly 15 minutes before sun exposure.
• Children under 6 months of age: ask a doctor.
• Reapply at least every 2 hours.
• Use a water-resistant sunscreen if swimming or sweating.

Keep out of reach of children.

PURPOSE

Sunscreen